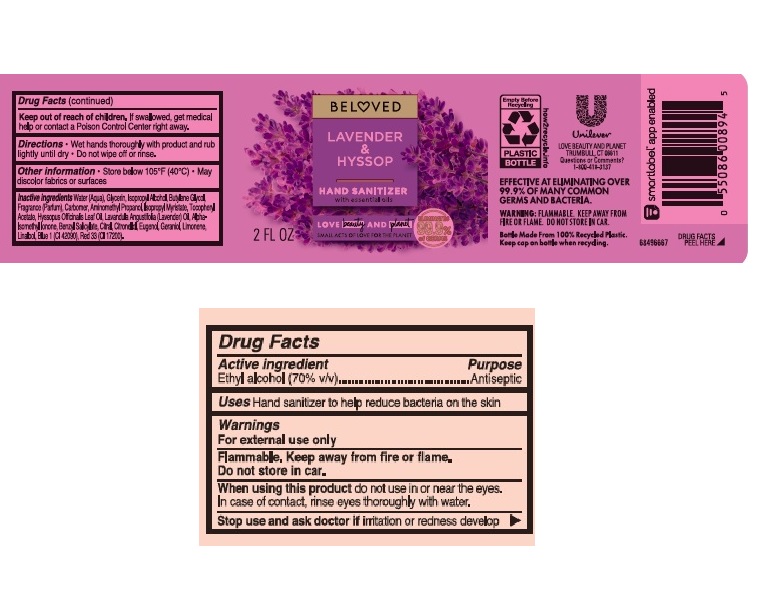 DRUG LABEL: Love Beauty and Planet
NDC: 64942-1839 | Form: GEL
Manufacturer: Conopco Inc. d/b/a/ Unilever
Category: otc | Type: HUMAN OTC DRUG LABEL
Date: 20241107

ACTIVE INGREDIENTS: ALCOHOL 700 mg/1 mL
INACTIVE INGREDIENTS: LIMONENE, (+)-; LINALOOL, (+/-)-; BUTYLENE GLYCOL; HYSSOP OIL; ISOPROPYL ALCOHOL; LAVENDER OIL; .ALPHA.-TOCOPHEROL ACETATE; CARBOMER HOMOPOLYMER, UNSPECIFIED TYPE; D&C RED NO. 33; AMINOMETHYLPROPANOL; WATER; GLYCERIN; ISOPROPYL MYRISTATE; .BETA.-CITRONELLOL, (R)-; FD&C BLUE NO. 1; BENZYL SALICYLATE; CITRAL; EUGENOL; GERANIOL; ISOMETHYL-.ALPHA.-IONONE

Love Beauty and Planet Beloved Lavender & Hyssop Hand Sanitizer

LOVE BEAUTY AND PLANET BELOVED LAVENDER & HYSSOP HAND SANITIZER - Ethyl Alcohol gel

Love Beauty and Planet Beloved Lavender & Hyssop Hand Sanitizer

Drug Facts

Active ingredient

Ethyl Alcohol 70 %

Purpose

Antiseptic

Uses

Hand sanitizer to help reduce bacteria on the skin

Warnings

For external use only
Flammable. Keep away from fire or flame. Do not store in car .
When using this product do not use in or near the eyes.
Stop use and ask doctor if irritation or redness develop.

• Keep out of reach of children except under adult supervision.

If swallowed, get medical help or contact a Poison Control Center right away.

Directions

Wet hands thoroughly with product and rub lightly until dry. Do not wipe off or rinse.

Other information

Store below 105˚F (40˚C). May discolor fabrics or surfaces.

Inactive ingredients

Water (Aqua), Glycerin, Isopropyl Alcohol, Butylene Glycol, Fragrance (Parfum), Carbomer, Aminomethyl Propanol, Isopropyl Myristate, Tocopheryl Acetate, Hyssopus Officinalis Leaf Oil, Lavandula Angustifolia (Lavender) Oil, Alpha-Isomethyl Ionone, Benzyl Salicylate, Citral, Citronellol, Eugenol, Limonene, Linalool, Blue 1 (CI 42090), Red 33 (CI 17200).

Questions or comments?

1-800-418-3137